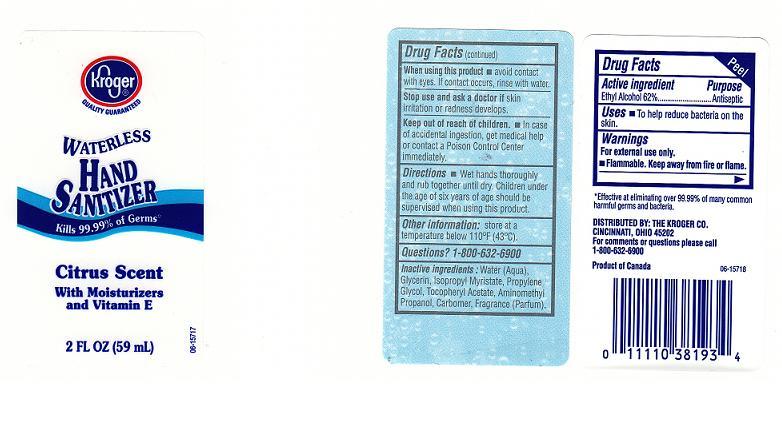 DRUG LABEL: WATERLESS HAND SANITIZER
NDC: 59450-231 | Form: GEL
Manufacturer: THE KROGER COMPANY
Category: otc | Type: HUMAN OTC DRUG LABEL
Date: 20110610

ACTIVE INGREDIENTS: ALCOHOL 62 mL/100 mL
INACTIVE INGREDIENTS: WATER; GLYCERIN; ISOPROPYL MYRISTATE; PROPYLENE GLYCOL; .ALPHA.-TOCOPHEROL ACETATE, DL-; AMINOMETHYLPROPANOL; CARBOMER 1342

DRUG FACTS

ACTIVE INGREDIENT

ETHYL ALCOHOL 62%

PURPOSE

ANTISEPTIC

USES

TO HELP REDUCE BACTERIA ON THE SKIN

WARNINGS

FOR EXTERNAL USE ONLY. FLAMMABLE.

WHEN USING THIS PRODUCT

AVOID CONTACT WITH EYES. IF CONTACT OCCURS RINSE WITH WATER.

STOP USE AND ASK A DOCTOR IF

SKIN IRRITATION OR REDNESS DEVELOPS.

KEEP OUT OF REACH OF CHILDREN

IN CASE OF ACCIDENTAL INGESTION, GET MEDICAL HELP OR CONTACT POISON CONTROL IMMEDIATELY.

DIRECTIONS

WET HANDS THOROUGHLY AND RUB HANDS UNTIL DRY. CHILDREN UNDER AGE OF SIX SHOULD BE SUPERVISED WHEN USING THIS PRODUCT.

OTHER INFORMATION

STORE AT ROOM TEMPERATURE.

QUESTIONS

1-800-632-6900

INACTIVE INGREDIENTS

WATER, GLYCERIN, ISOPROPYL MYRISTATE, PROPYLENE GLYCOL, TOCOPHERYL ACETATE, AMINOMETHYL PROPANOL, FRAGRANCE

PACKAGE LABEL

Enter section text here